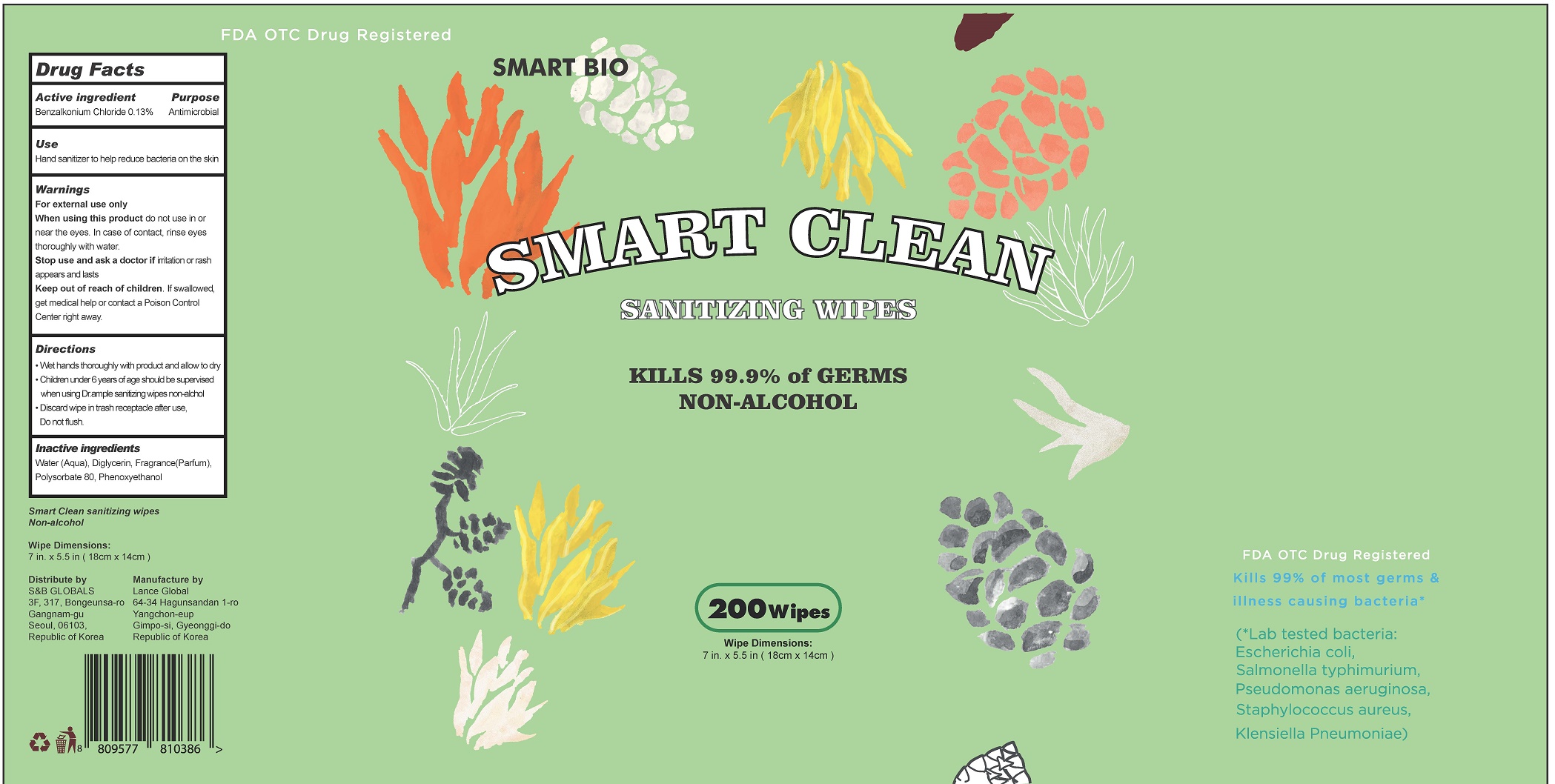 DRUG LABEL: SMART CLEAN SANITIZING WIPES
NDC: 79398-0002 | Form: CLOTH
Manufacturer: Lance Global Gimpo Branch
Category: otc | Type: HUMAN OTC DRUG LABEL
Date: 20210121

ACTIVE INGREDIENTS: BENZALKONIUM CHLORIDE 0.13 g/100 1
INACTIVE INGREDIENTS: WATER; PHENOXYETHANOL; POLYSORBATE 80

Lance Global Gimpo Branch

ACTIVE INGREDIENT

benzalkonium chloride

INACTIVE INGREDIENT

water, diglycerin, fragrance (parfum), polysorbate 80, phenoxyethanol

PURPOSE

hand sanitizer to help reduce bacteria on the skin

keep out of reach of the children

INDICATIONS AND USAGE

wet hands throughly with product and allow to dry

children unser 6 years of age should be supervised

discard wip in trash receptacle after use, do not flush

WARNINGS

For external use only

Do not use

- in children less than 2 months of age
- on open skin wounds

When using this product keep out of eyes, ears, and mouth. In case of contact with eyes, rinse eyes thoroughly with water.

Stop use and ask a doctor if irritation or rash occurs. These may be signs of serious condition.

Keep out of reach of children. If swallowed, get medical help or contact a Poison Control Center right away.

DOSAGE AND ADMINISTRATION

for external use only